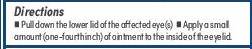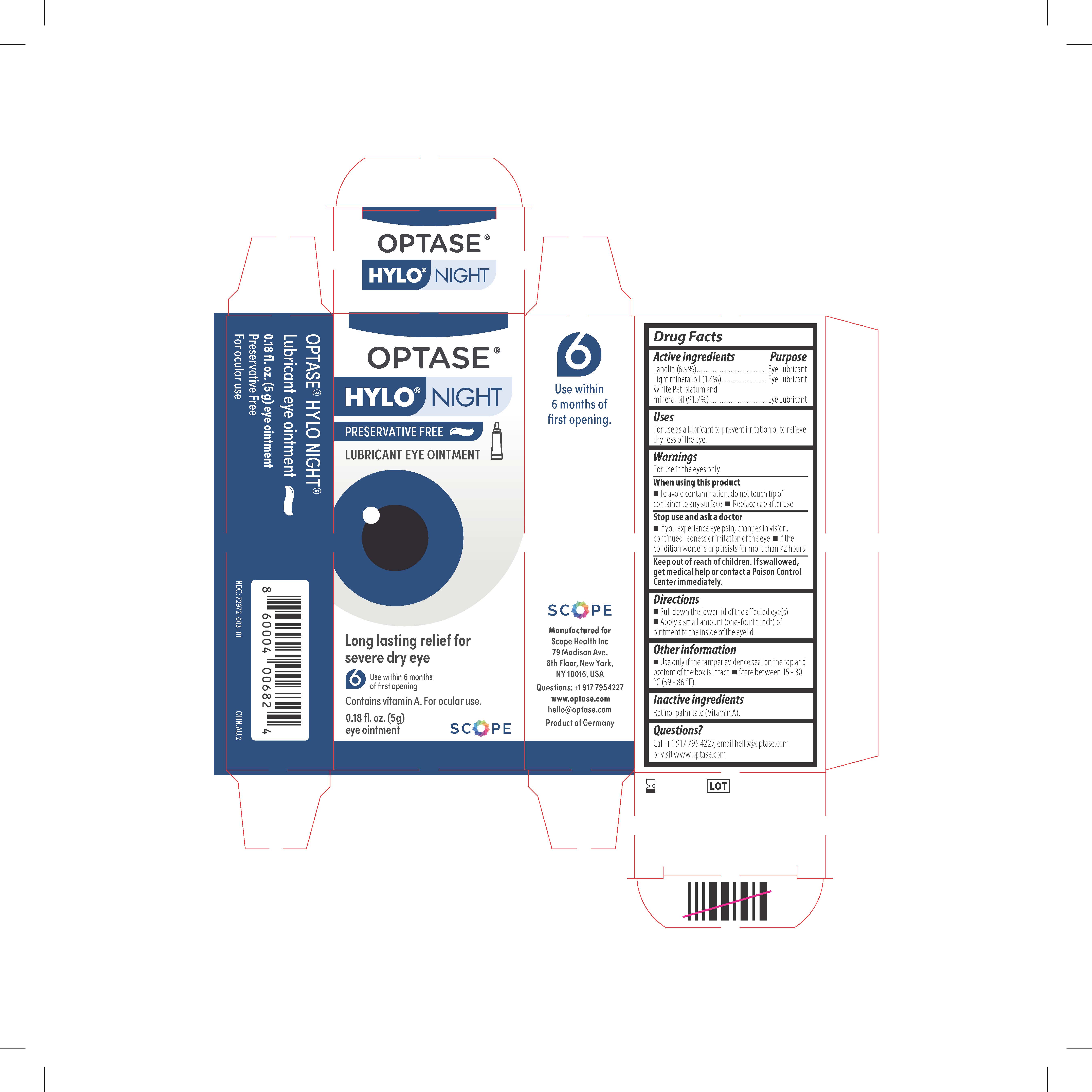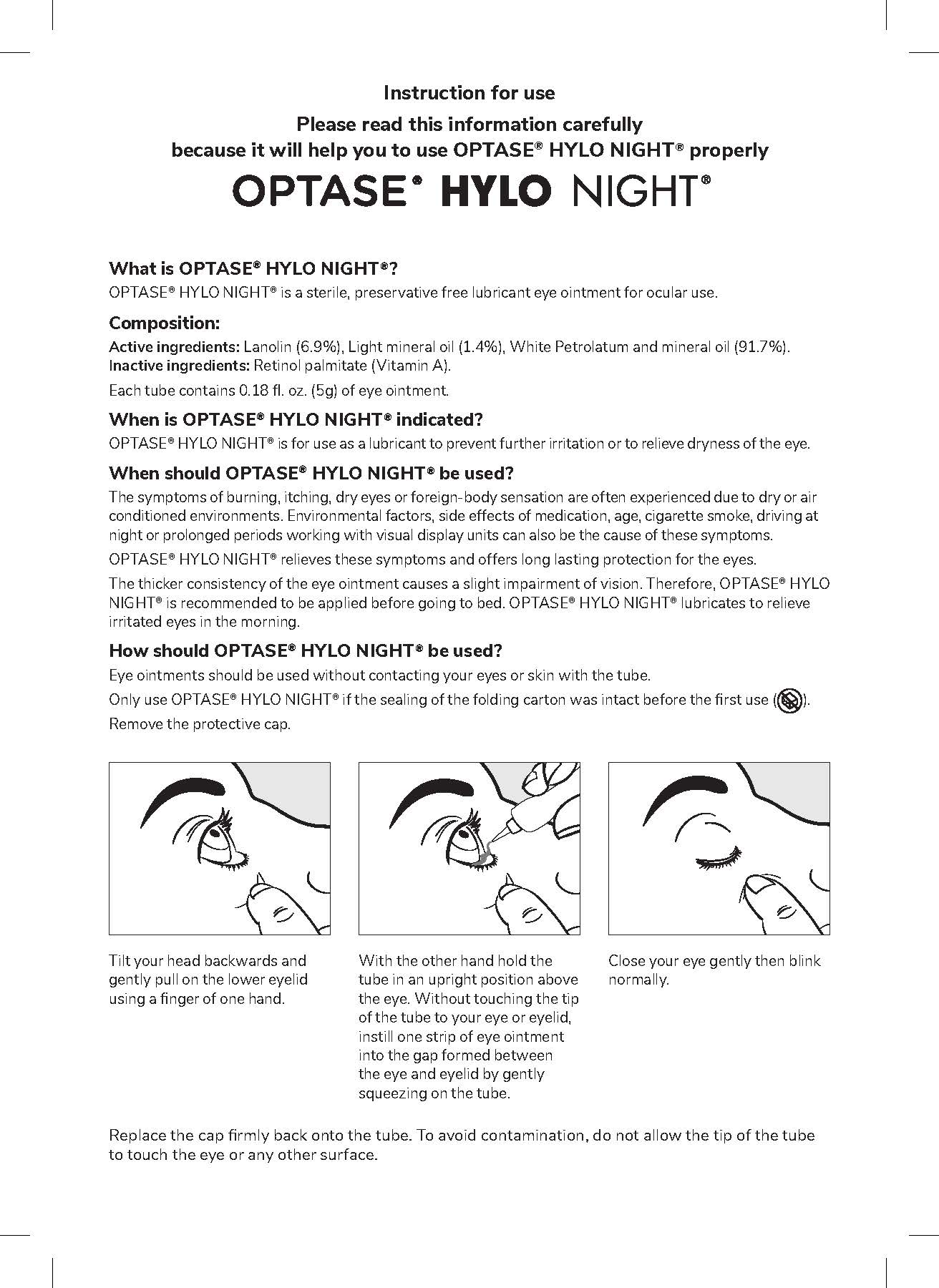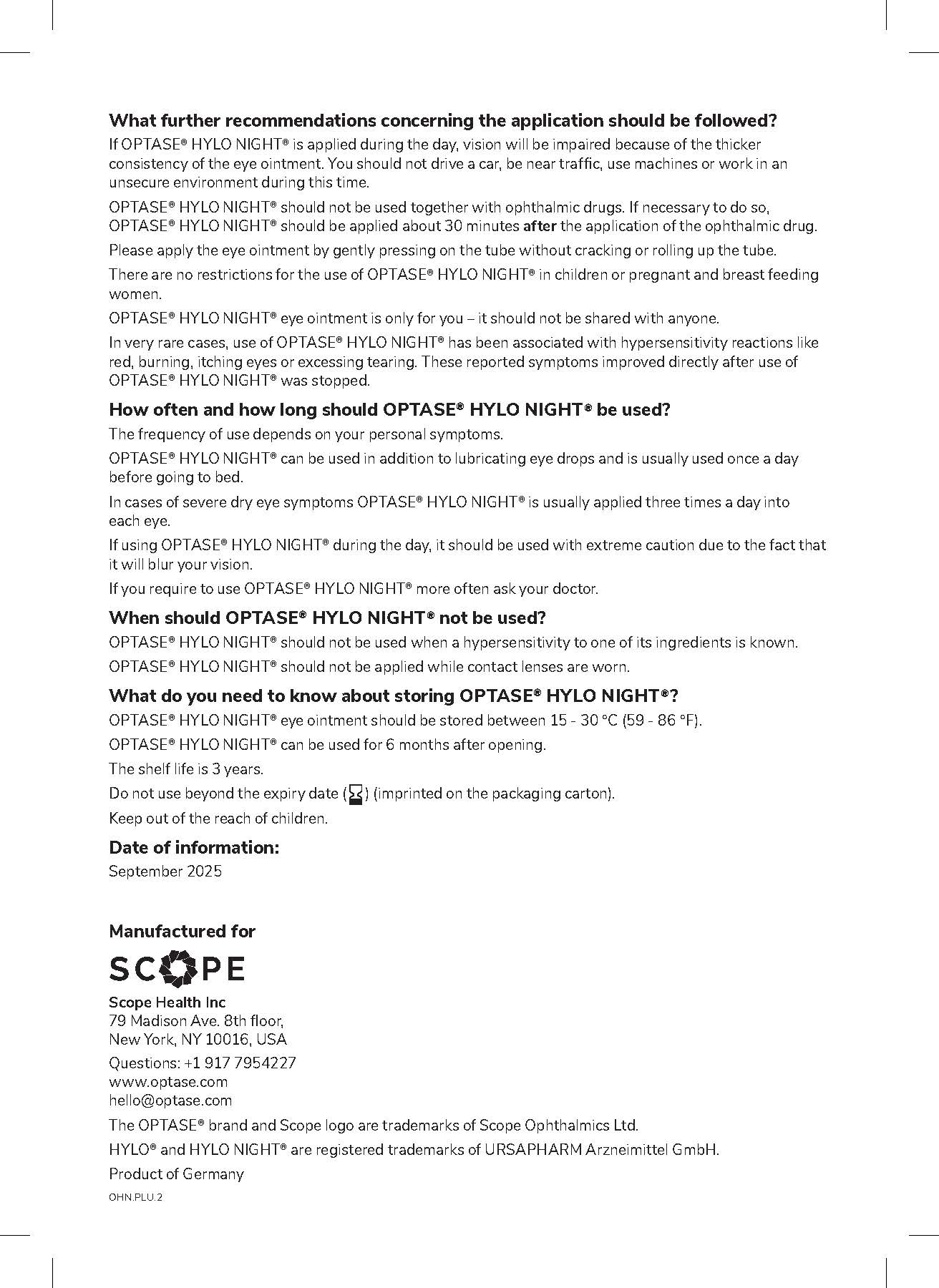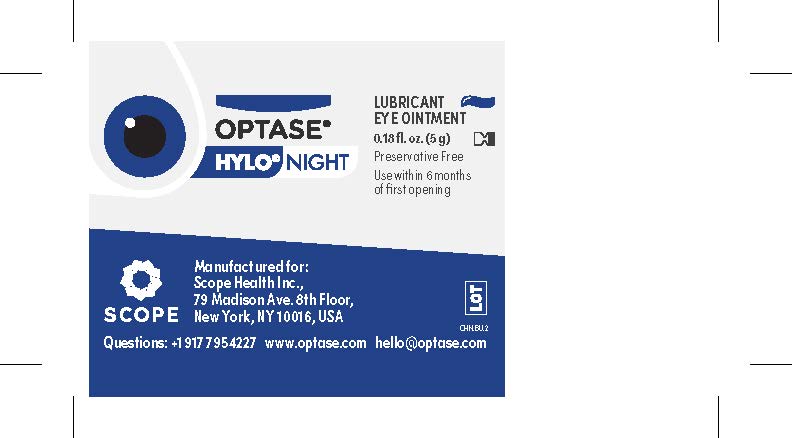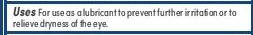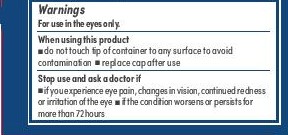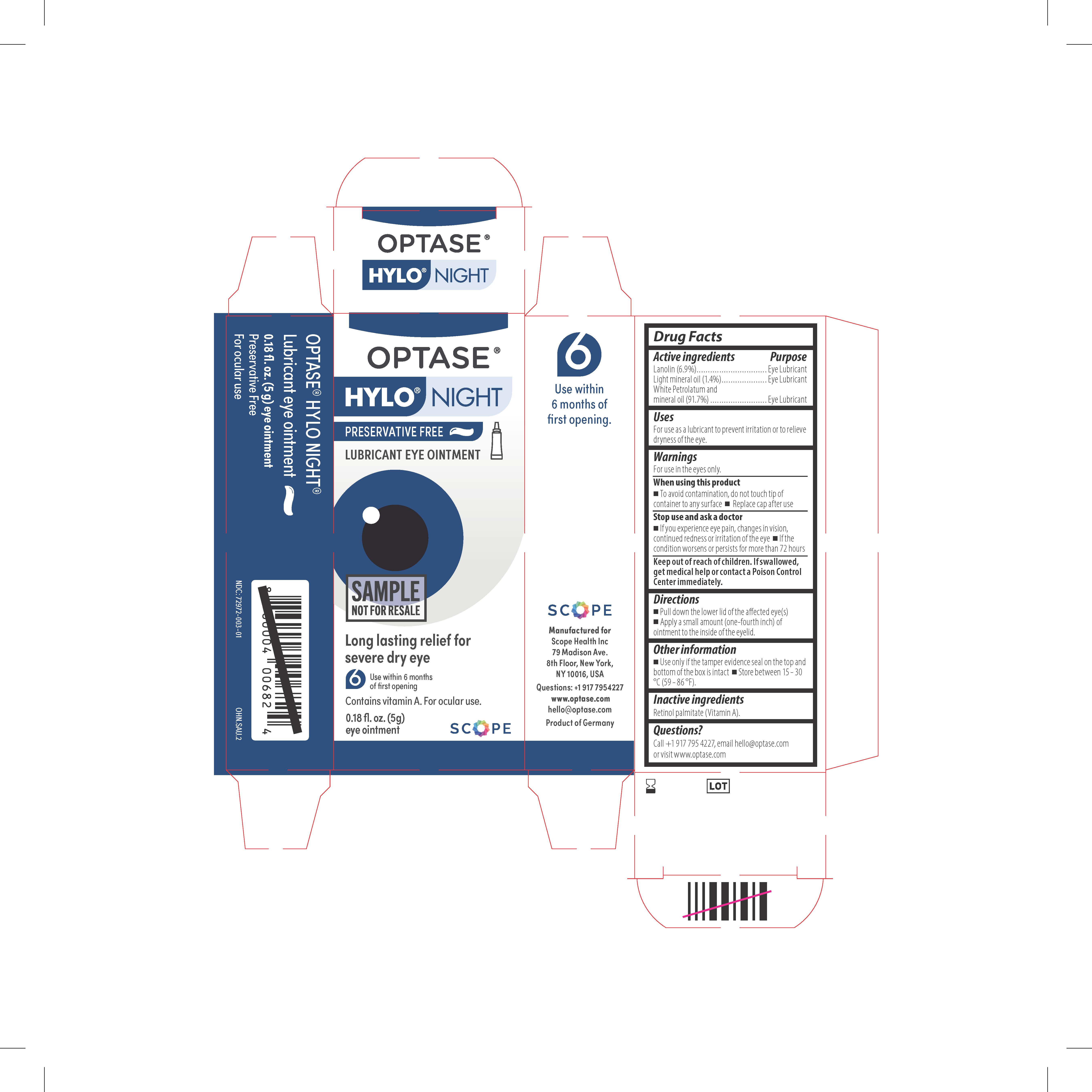 DRUG LABEL: Optase
NDC: 72972-003 | Form: OINTMENT
Manufacturer: Scope Health Inc
Category: otc | Type: HUMAN OTC DRUG LABEL
Date: 20260131

ACTIVE INGREDIENTS: PETROLATUM 0.9 g/1 g; LANOLIN 0.06 g/1 g
INACTIVE INGREDIENTS: LIGHT MINERAL OIL; VITAMIN A PALMITATE

Optase Hylo Night Eye Ointment

Keep Out of Reach of Children

If swallowed get medical
help or contact a poison
control center right away.

Inactive Ingredients

Retinol Palmitate (Vitamin A)

Active ingredients
White Petrolatum and
mineral oil (91.7%) . . . . . . . . . . . . . . . . . . . . . . . . . . . . . . .Eye Lubricant
Lanolin (6.9%) . . . . . . . . . . . . . . . . . . . . . . . . . . . . . . . . . . Eye Lubricant
Light mineral oil (1.4%) . . . . . . . . . . . . . . . . . . . . . . . . . . . Eye Lubricant

PURPOSE

Eye Lubricant